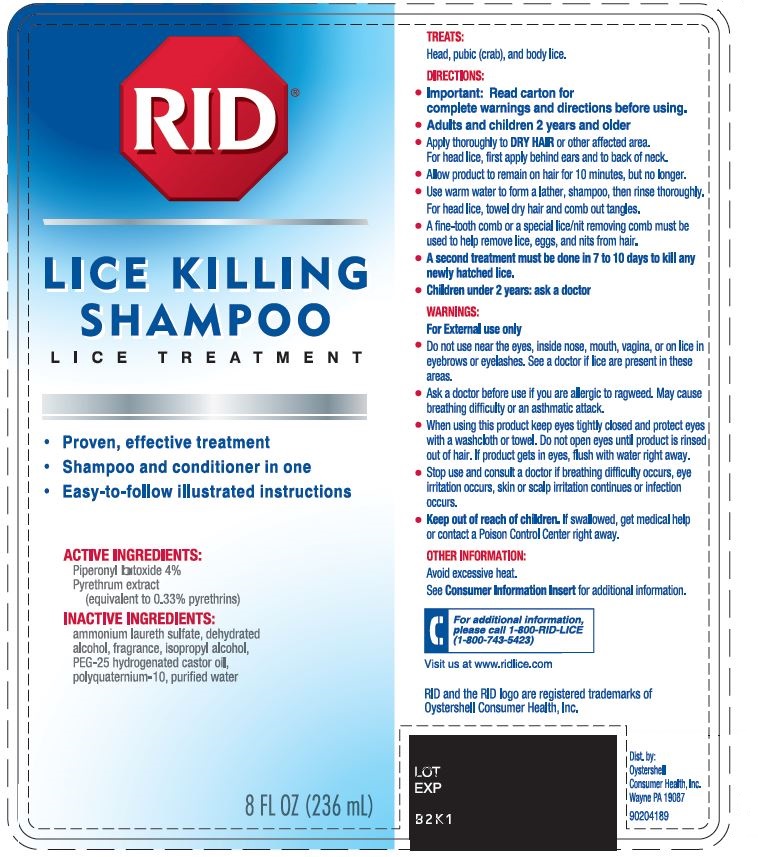 DRUG LABEL: RID Lice Killing
NDC: 82392-100 | Form: SHAMPOO
Manufacturer: Oystershell Consumer Health Inc
Category: otc | Type: HUMAN OTC DRUG LABEL
Date: 20231220

ACTIVE INGREDIENTS: Piperonyl butoxide 40 mg/1 mL; Pyrethrum extract 0.033 mg/1 mL
INACTIVE INGREDIENTS: Ammonium Laureth-2 Sulfate; Alcohol; Isopropyl Alcohol; Peg-25 Hydrogenated Castor Oil; Polyquaternium-10 (125 Mpa.S At 2%); Water

RID Lice Killing Shampoo

ACTIVE INGREDIENTS:

Piperonyl butoxide 4%
Pyrethrum extract (equivalent to 0.33% pyrethrins)

TREATS

Head, pubic (crab), and body lice.

INACTIVE INGREDIENTS:

ammonium laureth sulfate, dehydrated alcohol, fragrance, isopropyl alcohol, PEG-25 hydrogenated castor oil, polyquaternium-10, purified water

DIRECTIONS:

- Important: Read carton for complete warnings and directions before using.
- Adults and children 2 years and older
- Apply thoroughly to DRY HAIR or other affected area. For head lice, first apply behind ears and to back of neck.
- Allow product to remain on hair for 10 minutes, but no longer.
- Use warm water to form a lather, shampoo, then rinse thoroughly. For head lice, towel dry hair and comb out tangles.
- A fine-tooth comb or a special lice/nit removing comb must be used to help remove lice, eggs, and nits from hair.
- A second treatment must be done in 7-10 days to kill any newly hatched lice.
- Children under 2 years: ask a doctor

WARNINGS:

For external use only

- Do not use near the eyes, inside nose, mouth, vagina, or on lice in eyebrows or eyelashes. See a doctor if lice are present in these areas.

- Ask a doctor before use if you are allergic to ragweed. May cause breathing difficulty or an asthmatic attack.

- When using this product keep eyes tightly closed and protect eyes with a washcloth or towel. Do not open eyes until product is rinsed out of hair. If product gets in eyes, flush with water right away.

- Stop use and consult a doctor if breathing difficulty occurs, eye irritation occurs, skin or scalp irritation continues or infection occurs.

Keep out of reach of children. If swallowed, get medical help or contact a Poison Control Center right away.

Avoid excessive heat.
See Consumer Information Insert for additional information.
For additional information please call 1-800-RID-LICE (1-800-743-5423)
Visit us at www.ridlice.com
RID and the RID logo are registered trademarks of Oystershell Consumer Health, Inc.

PRINCIPAL DISPLAY PANEL

RID®
LICE KILLING SHAMPOO
Lice Treatment

- Proven, effective treatment
- Shampoo and conditioner in one
- East-to-follow illustrated instructions

8 FL OZ (236 mL)
LOT
EXP
B2K1